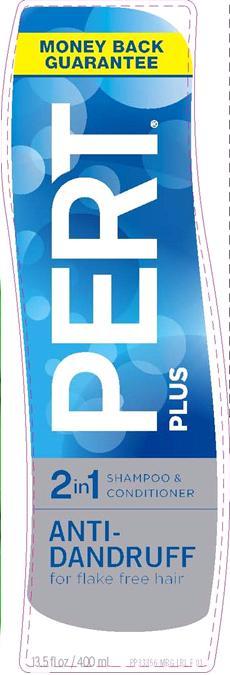 DRUG LABEL: Pert Plus 2 in 1 Shampoo and Conditioner
NDC: 41595-6502 | Form: SHAMPOO, SUSPENSION
Manufacturer: Idelle Labs, Ltd
Category: otc | Type: HUMAN OTC DRUG LABEL
Date: 20120604

ACTIVE INGREDIENTS: PYRITHIONE ZINC 1 mL/100 mL
INACTIVE INGREDIENTS: WATER; AMMONIUM LAURETH-5 SULFATE; AMMONIUM LAURYL SULFATE; GLYCOL DISTEARATE; DIMETHICONE; CETYL ALCOHOL; COCO MONOETHANOLAMIDE; SODIUM CHLORIDE; GUAR HYDROXYPROPYLTRIMONIUM CHLORIDE (1.7 SUBSTITUENTS PER SACCHARIDE); HYDROGENATED POLYDECENE (550 MW); SODIUM CITRATE; SODIUM BENZOATE; POLYQUATERNIUM-10 (400 CPS AT 2%); POLYETHYLENE GLYCOL 7000; TRIMETHYLOLPROPANE TRICAPRYLATE/TRICAPRATE; CITRIC ACID MONOHYDRATE; BENZYL ALCOHOL; METHYLCHLOROISOTHIAZOLINONE; METHYLISOTHIAZOLINONE; AMMONIUM XYLENESULFONATE; FD&C BLUE NO. 1; D&C YELLOW NO. 10

Pert Plus 2 in 1 Shampoo and Conditioner Anti-Dandruff

Pert Plus 2 in 1 Shampoo and Conditioner Anti-Dandruff
for flake-free hair
Great hair should be simple
Use daily: 1. Wet 2. Lather 3. Rinse.
MM1

Active Ingredient

Pyrithione Zinc 1.0%

Purpose:

Anti-Dandruff

Uses

Controls the symptoms of dandruff.

Warning:

For external use only

When using this product

avoid contact with eyes. If contact occurs, rinse eyes thoroughly with water.

Stop use and ask a doctor

if condition worsens or does not improve after regular use of this product as directed.

Keep this and all drugs out of reach of children.

If swallowed, get medical help or contact a Poison Control Center right away.

Directions:

For best results, use at least twice a week or as directed by a doctor. Gently massage into wet hair, lather and rinse. Repeat if desired.

Inactive Ingredients:

Water, ammonium laureth sulfate, ammonium lauryl sulfate, glycol distearate, dimethicone, cetyl alcohol, cocamide MEA, sodium chloride, fragrance, guar hydroxypropyltrimonium chloride, hydrogenated polydecene, sodium citrate, sodium benzoate, polyquaternium 10, PEG-7M, trimethylolpropane tricaprylate/tricaprate, citric acid, benzyl alcohol, methylchloroisothiazolinone, methylisothiazolinone, ammonium xylene sulfonate, Yellow 10, Blue 1.

Questions or Comments?

1-800-487-7273
www.pertplus.com

Idelle Labs, Ltd. All rights reserved
Made in Canada. Distributed by Idelle Labs, Ltd., El Paso, TX 79912

label